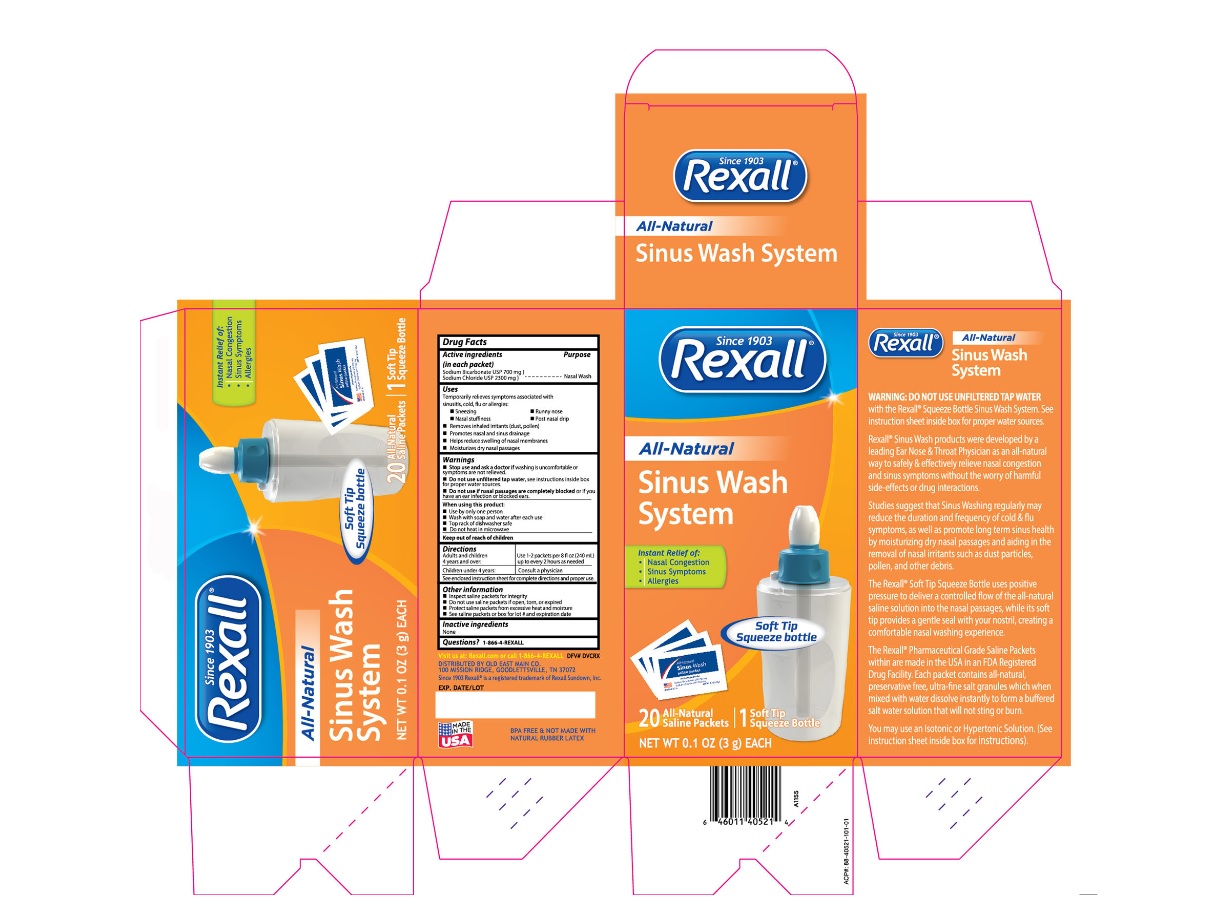 DRUG LABEL: Rexall Sinus Wash System
NDC: 55910-919 | Form: KIT | Route: NASAL
Manufacturer: Dolgencorp, LLC
Category: otc | Type: HUMAN OTC DRUG LABEL
Date: 20251210

ACTIVE INGREDIENTS: SODIUM CHLORIDE 2300 mg/3000 mg; SODIUM BICARBONATE 700 mg/3000 mg
INACTIVE INGREDIENTS: WATER

Rexall Sinus Wash System/Kit- Soft Tip Squeeze bottle

Active ingredients

(in each packet)

Sodium Bicarbonate USP (700 mg)

Sodium Chloride USP (2300 mg)

Purpose

Nasal Wash

Uses

Temporarily relieves symptoms associated with

sinusitis, cold, flu or allergies

-Sneezing

-Nasal Stuffiness

-Runny nose

-Post nasal drip

Removes inhaled irritants (dust, pollen)

Promotes nasal and sinus drainage

Helps reduce swelling of nasal membranes

Moisturizes dry nasal passages

Keep out of reach of children

Warnings

Stop use and ask a doctor if washing is uncomfortable

or symptoms are not relieved.

Do not use unfiltered tap water. see instructions inside box for proper water sources

Do not use if nasal passages are completely blocked or if you have an ear infection or blocked ears.

Directions

Adults and children 4 years and over: Use 1-2 packets per 8 fl oz (240 mL) up to every 2 hours as needed.

Children under 4 years: Consult a physician

See enclosed instruction sheet for complete directions and proper use.

Other Information

-Inspect saline packets for integrity

-Do not use saline packets if open or torn

-Protect saline packets form excessive heat and moisture

-See saline packets or box for lot number and expiration date

Questions?

1-888-4-REXALL

Inactive Ingredients

None

Instructions for Use of the SinuCleanse Squeeze

Directions: Read through entire section before using for the first time.

1. Remove the cap from the SinuCleanse Squeeze bottle.

2. Pour the pre-mixed saline dry ingredients into the SinuCleanse Squeeze

Bottle. First-time users should start with 1 packet of the saline dry

ingredients. As you become more accustomed to the system, work up

to using 2 full packets. Additional packets may be purchased from your

nearest pharmacy.

3. Fill the bottle with a proper water source * leaving approximately 1/2 inch

of air at the top of the bottle. This makes 1 cup (8 oz.) of solution.

4. Tighten the cap on the bottle securely, place one finger over the tip of the cap and gently

shake the bottle until the dry ingredients have completely dissolved.

5. Lean over the sink with your head bent down so you are looking directly into the basin. Place

the tip of the cap up to the right nostril and gently insert the tip so that it forms a comfortable

seal. Aim the tip at the back of your head, not at the top of your head.

6. Squeeze the bottle gently so that the solution enters the right nostril. Do not inhale or "snort"

the solution into the nose - breathe through your mouth.

7. In a few moments the solution will begin to drain out of the left nostril. Continue to squeeze

the bottle gently until you have used approximately half of the solution.

8. Remove the tip of the bottle from your nostril, then exhale through both nostrils

to clear them of excess mucus and solution. Gently blow your nose into a tissue.

9. Repeat the procedure on the left nostril with the remaining solution.

10. A small amount of solution will remain at the bottom of the bottle. Discard the

remaining solution.

11. Thoroughly rinse the bottle after each use with water that has been distilled,

sterilized, filtered or previously boiled and leave the bottle open to air dry

completely. The SinuCleanse Squeeze Bottle is also top-rack dishwasher safe.

Hints for a more comfortable nasal wash

- Begin using the SinuCleanse System slowly. A full pot or bottle of solution

on each side is not necessary to receive the full benefit.

-If the solution is too warm or too cold, the nasal wash will be uncomfortable.

-If stinging or irritation occurs, try using 1/2 of a packet of dry ingredients for the Neti

Pot or 1 packet per Squeeze Bottle of the saline dry ingredients. Gradually work up

to using the solution at full strength. Do not use less than 1/2 packet for the Neti Pot

or 1 packet per Squeeze bottle.

-If you experience ear discomfort after use, try to blow your nose more gently after the

wash. If the problem persists, the openings of your Eustachian tubes may be

particularly wide and the use of the SinuCleanse System may need

to be discontinued.

-Breathe continuously through the mouth when using the SinuCleanse system

to avoid solution draining from the back of the nose into the mouth.

-Some people experience irritation of the skin just insdie the nostrils with repeated

nasal washing. Applying a thin layer of aloe to the inside of the nostrils before or after

the nasal wash will be soothing.